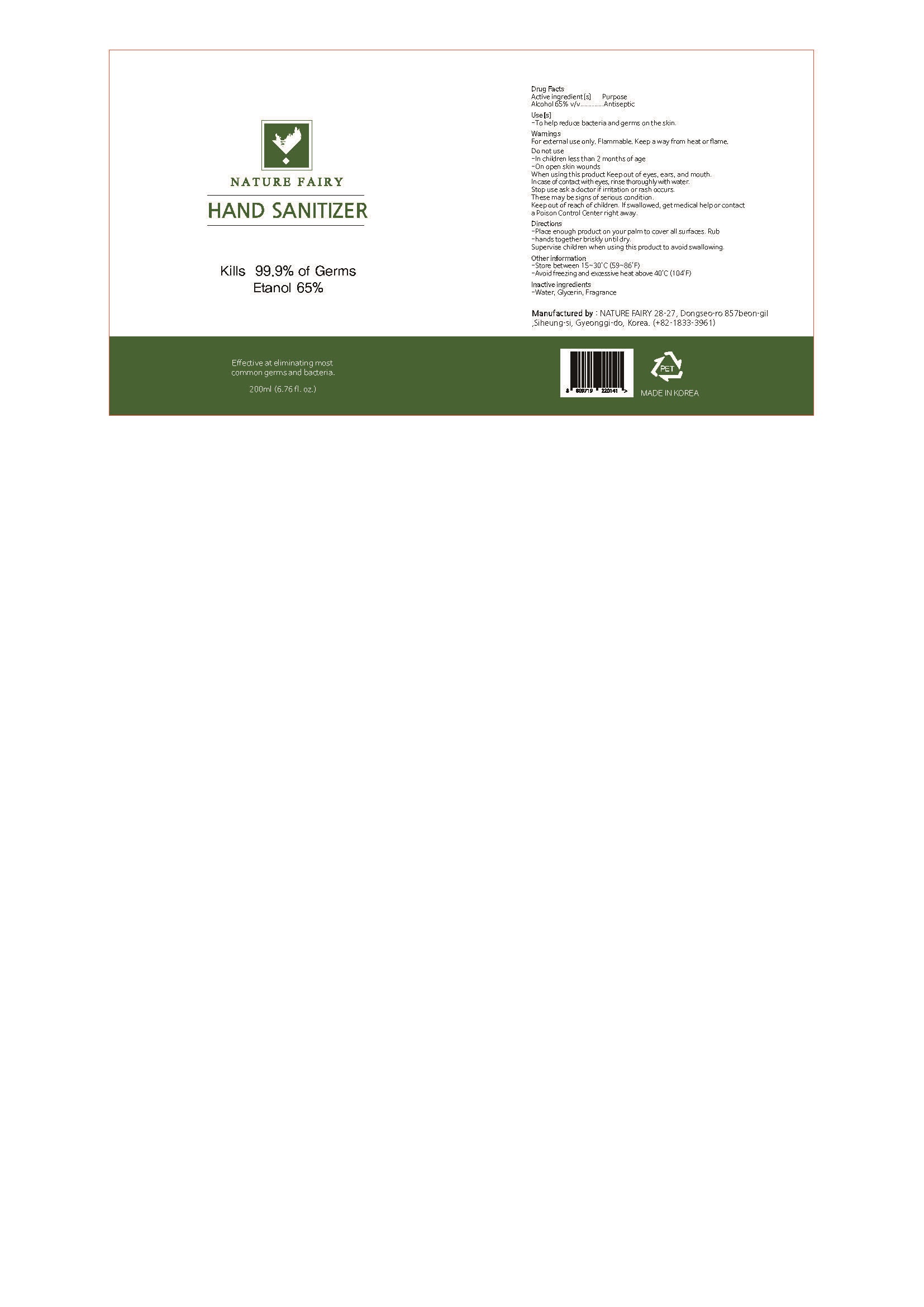 DRUG LABEL: HAND SANITIZER
NDC: 78855-0002 | Form: LIQUID
Manufacturer: Nature Fairy Co., Ltd
Category: otc | Type: HUMAN OTC DRUG LABEL
Date: 20200621

ACTIVE INGREDIENTS: ALCOHOL 65 mL/100 mL
INACTIVE INGREDIENTS: GLYCERIN; WATER

Drug Facts

ACTIVE INGREDIENT

alcohol

INACTIVE INGREDIENT

Water, Glycerin, Fragrance

PURPOSE

To help reduce bacteria and germs on the skin

KEEP OUT OF REACH OF THE CHILDREN

INDICATIONS AND USAGE

Apply to clean, dry hands. Apply sufficient amount to thoroughly wet all surfaces of hands and fingers. Rub onto hands until dry.

Supervise children in the use of this product.

Dispense appropriate amount on your palm and thoroughly spread on both hands and rub into the skin until dry

WARNINGS

For external use only.

Flammable, keep away from fire or flame.

When using this product keep out of eyes. If contact with eyes occurs, rinse promptly and thoroughly with water.

Stop use and ask a doctor if significant irritation or sensitization develops.

Keep out of reach of children. If swallowed, get medical help or contact a Poison Control Center right away.

DOSAGE AND ADMINISTRATION

for external use only